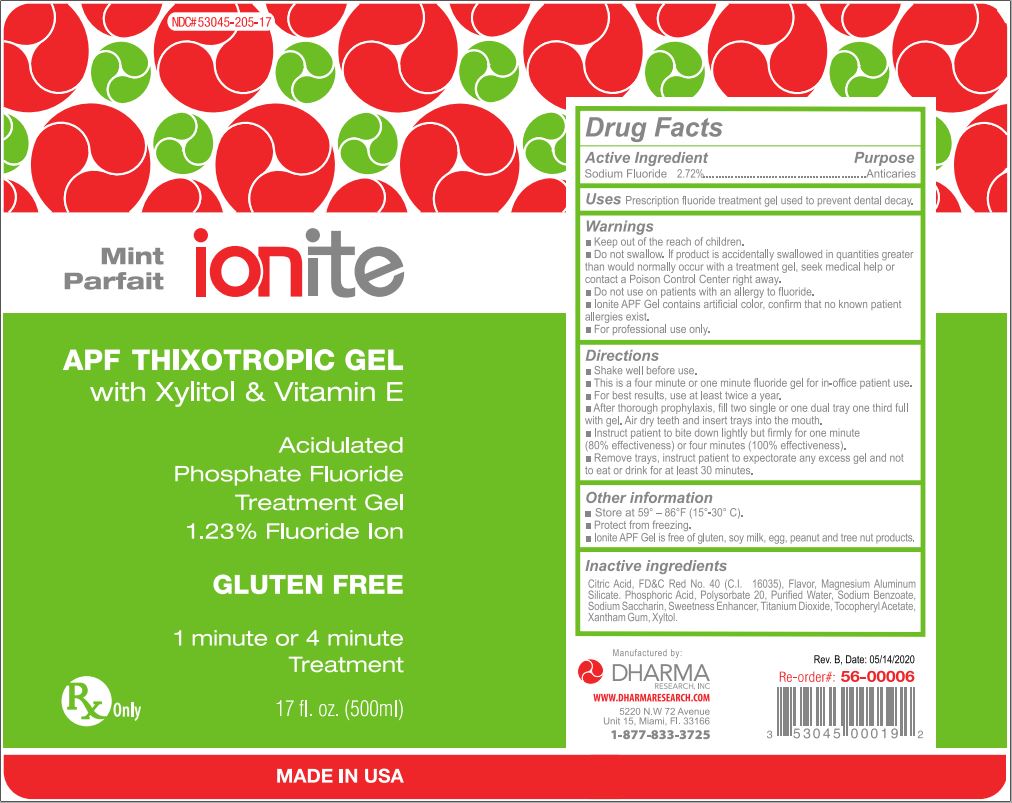 DRUG LABEL: Ionite APF
NDC: 53045-205 | Form: GEL
Manufacturer: Dharma Research, Inc.
Category: prescription | Type: HUMAN PRESCRIPTION DRUG LABEL
Date: 20210220

ACTIVE INGREDIENTS: SODIUM FLUORIDE 6.027 g/490 g
INACTIVE INGREDIENTS: WATER; MAGNESIUM ALUMINUM SILICATE; FD&C RED NO. 40; SACCHARIN SODIUM; SODIUM BENZOATE; TITANIUM DIOXIDE; XYLITOL; ANHYDROUS CITRIC ACID; .ALPHA.-TOCOPHEROL ACETATE; XANTHAN GUM; CARBOMER HOMOPOLYMER TYPE C; PHOSPHORIC ACID; HYDROFLUORIC ACID

STORAGE AND HANDLING

- Store at 59o - 86oF (15o - 30oC)
- Protect from freezing
- Ionite APF Gel is free of gluten, soymilk, egg peanut and free of nut products

INACTIVE INGREDIENT

Citric Acid, F D & C Red No. 40 (C.I. 16035), Flavor, Hydrofluoric Acid, Magnesium Aluminum Silicate, Phosphoric Acid, Polysorbate 20, Purified Water, Sodium Benzoate, Sodium Saccharin, Sweetness Enhancer, Titanium Dioxide, Tocopheryl Acetate, Xanthan Gum, Xylitol.

WARNINGS AND PRECAUTIONS

- Keep out of the reach of children.
- Do not swallow. If product is accidentally swallowed in quantities greater than would normally occur with a treatment gel, seek medical help or contact a Poison Control Center right away.
- Do not use on patients with an allergy Fluoride.
- Ionite APF Gel contains artificial color, confirm that no kno.wn patient allergies exist.
- For professional use only.

- Shake well before use.
- This is a four minute or one minute Fluoride gel for in-office patient use.
- For best results, use at least twice a year.
- After thorough prophylaxis, fill two single or one dual tray one third full with gel. Air dry teeth and insert trays into the mouth.
- Instruct patient to bite down lightly but firmly for one minute (80% effectiveness) or four minutes (100% effectiveness)
- Remove trays, instruct patient to expectorate any excess gel and not to eat or drink for at least 30 minutes